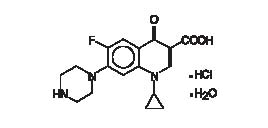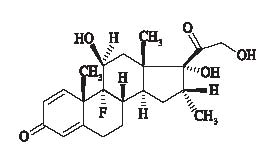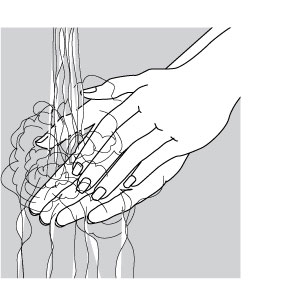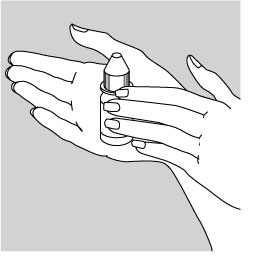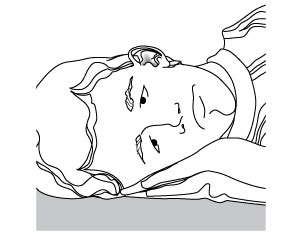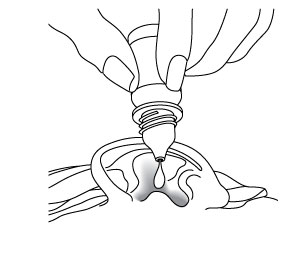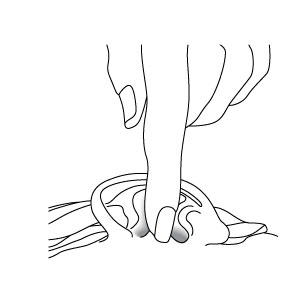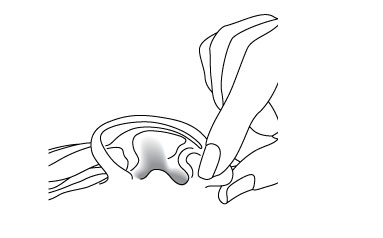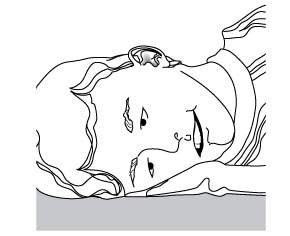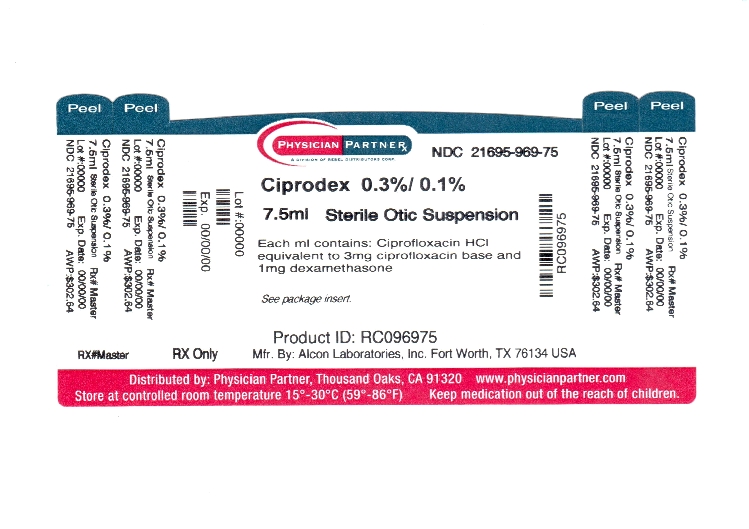 DRUG LABEL: CIPRODEX
NDC: 21695-969 | Form: SUSPENSION
Manufacturer: Rebel Distributors Corp
Category: prescription | Type: HUMAN PRESCRIPTION DRUG LABEL
Date: 20110823

ACTIVE INGREDIENTS: CIPROFLOXACIN HYDROCHLORIDE 3 mg/1 mL; DEXAMETHASONE 1 mg/1 mL
INACTIVE INGREDIENTS: BENZALKONIUM CHLORIDE; BORIC ACID; SODIUM CHLORIDE; TYLOXAPOL; ACETIC ACID; SODIUM ACETATE; EDETATE DISODIUM; WATER; SODIUM HYDROXIDE; HYDROCHLORIC ACID

CIPRODEX®
(ciprofloxacin 0.3% and dexamethasone 0.1%)
Sterile Otic Suspension

DESCRIPTION

CIPRODEX® (ciprofloxacin 0.3% and dexamethasone 0.1%) Sterile Otic Suspension contains the synthetic broad-spectrum antibacterial agent, ciprofloxacin hydrochloride, combined with the anti-inflammatory corticosteroid, dexamethasone, in a sterile, preserved suspension for otic use. Each mL of CIPRODEX® Otic contains ciprofloxacin hydrochloride (equivalent to 3 mg ciprofloxacin base), 1 mg dexamethasone, and 0.1 mg benzalkonium chloride as a preservative. The inactive ingredients are boric acid, sodium chloride, hydroxyethyl cellulose, tyloxapol, acetic acid, sodium acetate, edetate disodium, and purified water. Sodium hydroxide or hydrochloric acid may be added for adjustment of pH.

Ciprofloxacin, a fluoroquinolone is available as the monohydrochloride monohydrate salt of 1-cyclopropyl-6-fluoro-1,4-dihydro-4-oxo-7-(1-piperazinyl)-3-qui nolinecarboxylic acid. The empirical formula is C17H18FN3O3·HCl·H2O and the structural formula is:

Dexamethasone,

9-fluoro-11(beta),17,21-trihydroxy-16(alpha)-methylpregna-1,4-di ene-3,20-dione, is an anti-inflammatory corticosteroid. The empirical formula is C22H29FO5 and the structural formula is:

CLINICAL PHARMACOLOGY

Pharmacokinetics: Following a single bilateral 4-drop (total dose = 0.28 mL, 0.84 mg ciprofloxacin, 0.28 mg dexamethasone) topical otic dose of CIPRODEX® Otic to pediatric patients after tympanostomy tube insertion, measurable plasma concentrations of ciprofloxacin and dexamethasone were observed at 6 hours following administration in 2 of 9 patients and 5 of 9 patients, respectively.

Mean ± SD peak plasma concentrations of ciprofloxacin were 1.39 ± 0.880 ng/mL (n=9). Peak plasma concentrations ranged from 0.543 ng/mL to 3.45 ng/mL and were on average approximately 0.1% of peak plasma concentrations achieved with an oral dose of 250-mg [1]. Peak plasma concentrations of ciprofloxacin were observed within 15 minutes to 2 hours post dose application.

Mean ± SD peak plasma concentrations of dexamethasone were 1.14 ± 1.54 ng/mL (n=9). Peak plasma concentrations ranged from 0.135 ng/mL to 5.10 ng/mL and were on average approximately 14% of peak concentrations reported in the literature following an oral 0.5-mg tablet dose[2]. Peak plasma concentrations of dexamethasone were observed within 15 minutes to 2 hours post dose application.

Dexamethasone has been added to aid in the resolution of the inflammatory response accompanying bacterial infection (such as otorrhea in pediatric patients with AOM with tympanostomy tubes).

Microbiology: Ciprofloxacin has in vitro activity against a wide range of gram-positive and gram-negative microorganisms. The bactericidal action of ciprofloxacin results from interference with the enzyme, DNA gyrase, which is needed for the synthesis of bacterial DNA. Cross-resistance has been observed between ciprofloxacin and other fluoroquinolones. There is generally no cross-resistance between ciprofloxacin and other classes of antibacterial agents such as beta-lactams or aminoglycosides.

Ciprofloxacin has been shown to be active against most isolates of the following microorganisms, both in vitro and clinically in otic infections as described in the INDICATIONS AND USAGE section.

Aerobic and facultative gram-positive microorganisms

Staphylococcus aureus

Streptococcus pneumoniae

Aerobic and facultative gram-negative microorganisms

Haemophilus influenzae

Moraxella catarrhalis

Pseudomonas aeruginosa

INDICATIONS AND USAGE

CIPRODEX® Otic is indicated for the treatment of infections caused by susceptible isolates of the designated microorganisms in the specific conditions listed below:

Acute Otitis Media in pediatric patients (age 6 months and older) with tympanostomy tubes due to Staphylococcus aureus, Streptococcus pneumoniae, Haemophilus influenzae, Moraxella catarrhalis, and Pseudomonas aeruginosa.

Acute Otitis Externa in pediatric (age 6 months and older), adult and elderly patients due to Staphylococcus aureus and Pseudomonas aeruginosa.

CONTRAINDICATIONS

CIPRODEX® Otic is contraindicated in patients with a history of hypersensitivity to ciprofloxacin, to other quinolones, or to any of the components in this medication. Use of this product is contraindicated in viral infections of the external canal including herpes simplex infections.

WARNINGS

FOR OTIC USE ONLY

(This product is not approved for ophthalmic use.)

NOT FOR INJECTION

CIPRODEX® Otic should be discontinued at the first appearance of a skin rash or any other sign of hypersensitivity. Serious and occasionally fatal hypersensitivity (anaphylactic) reactions, some following the first dose, have been reported in patients receiving systemic quinolones. Serious acute hypersensitivity reactions may require immediate emergency treatment.

PRECAUTIONS

General:

As with other antibacterial preparations, use of this product may result in overgrowth of nonsusceptible organisms, including yeast and fungi. If the infection is not improved after one week of treatment, cultures should be obtained to guide further treatment. If otorrhea persists after a full course of therapy, or if two or more episodes of otorrhea occur within six months, further evaluation is recommended to exclude an underlying condition such as cholesteatoma, foreign body, or a tumor.

The systemic administration of quinolones, including ciprofloxacin at doses much higher than given or absorbed by the otic route, has led to lesions or erosions of the cartilage in weight-bearing joints and other signs of arthropathy in immature animals of various species.

Guinea pigs dosed in the middle ear with CIPRODEX® Otic for one month exhibited no drug-related structural or functional changes of the cochlear hair cells and no lesions in the ossicles. CIPRODEX® Otic was also shown to lack dermal sensitizing potential in the guinea pig when tested according to the method of Buehler.

No signs of local irritation were found when CIPRODEX® Otic was applied topically in the rabbit eye.

Information for Patients

For otic use only. (This product is not approved for use in the eye.) Warm the bottle in your hand for one to two minutes prior to use and shake well immediately before using.

Avoid contaminating the tip with material from the ear, fingers, or other sources.

Protect from light.

If rash or allergic reaction occurs, discontinue use immediately and contact your physician.

It is very important to use the ear drops for as long as the doctor has instructed, even if the symptoms improve.

Discard unused portion after therapy is completed.

Acute Otitis Media in pediatric patients with tympanostomy tubes Prior to administration of CIPRODEX® Otic in patients (6 months and older) with acute otitis media through tympanostomy tubes, the suspension should be warmed by holding the bottle in the hand for one or two minutes to avoid dizziness which may result from the instillation of a cold suspension. The patient should lie with the affected ear upward, and then the drops should be instilled. The tragus should then be pumped 5 times by pushing inward to facilitate penetration of the drops into the middle ear. This position should be maintained for 60 seconds. Repeat, if necessary, for the opposite ear (see DOSAGE AND ADMINISTRATION).

Acute Otitis Externa

Prior to administration of CIPRODEX® Otic in patients with acute otitis externa, the suspension should be warmed by holding the bottle in the hand for one or two minutes to avoid dizziness which may result from the instillation of a cold suspension. The patient should lie with the affected ear upward, and then the drops should be instilled. This position should be maintained for 60 seconds to facilitate penetration of the drops into the ear canal. Repeat, if necessary, for the opposite ear (see DOSAGE AND ADMINISTRATION).

Drug Interactions

Specific drug interaction studies have not been conducted with CIPRODEX® Otic.

Carcinogenesis, Mutagenesis, Impairment of Fertility

Long-term carcinogenicity studies in mice and rats have been completed for ciprofloxacin. After daily oral doses of 750 mg/kg (mice) and 250 mg/kg (rats) were administered for up to 2 years, there was no evidence that ciprofloxacin had any carcinogenic or tumorigenic effects in these species. No long term studies of CIPRODEX® Otic have been performed to evaluate carcinogenic potential.

Eight in vitro mutagenicity tests have been conducted with ciprofloxacin, and the test results are listed below:

Salmonella/Microsome Test (Negative)

E. coli DNA Repair Assay (Negative)

Mouse Lymphoma Cell Forward Mutation

Assay (Positive)

Chinese Hamster V79 Cell HGPRT Test (Negative)

Syrian Hamster Embryo Cell Transformation

Assay (Negative)

Saccharomyces cerevisiae Point Mutation

Assay (Negative)

Saccharomyces cerevisiae Mitotic Crossover and Gene

Conversion Assay (Negative)

Rat Hepatocyte DNA Repair Assay (Positive)

Thus, 2 of the 8 tests were positive, but results of the following 3 in vivo test systems gave negative results:

Rat Hepatocyte DNA Repair Assay

Micronucleus Test (Mice)

Dominant Lethal Test (Mice)

Fertility studies performed in rats at oral doses of ciprofloxacin up to 100 mg/kg/day revealed no evidence of impairment. This would be over 100 times the maximum recommended clinical dose of ototopical ciprofloxacin based upon body surface area, assuming total absorption of ciprofloxacin from the ear of a patient treated with CIPRODEX® Otic twice per day according to label directions.

Long term studies have not been performed to evaluate the carcinogenic potential of topical otic dexamethasone. Dexamethasone has been tested for in vitro and in vivo genotoxic potential and shown to be positive in the following assays; chromosomal aberrations, sister-chromatid exchange in human lymphocytes and micronuclei and sister-chromatid exchanges in mouse bone marrow. However, the Ames/Salmonella assay, both with and without S9 mix, did not show any increase in His+ revertants.

The effect of dexamethasone on fertility has not been investigated following topical otic application. However, the lowest toxic dose of dexamethasone identified following topical dermal application was 1.802 mg/kg in a 26-week study in male rats and resulted in changes to the testes, epididymis, sperm duct, prostate, seminal vessicle, Cowper's gland and accessory glands. The relevance of this study for short term topical otic use is unknown.

Pregnancy

Teratogenic Effects. Pregnancy Category C:

Reproduction studies have been performed in rats and mice using oral doses of up to 100 mg/kg and IV doses up to 30 mg/kg and have revealed no evidence of harm to the fetus as a result of ciprofloxacin. In rabbits, ciprofloxacin (30 and 100 mg/kg orally) produced gastrointestinal disturbances resulting in maternal weight loss and an increased incidence of abortion, but no teratogenicity was observed at either dose. After intravenous administration of doses up to 20 mg/kg, no maternal toxicity was produced in the rabbit, and no embryotoxicity or teratogenicity was observed.

Corticosteroids are generally teratogenic in laboratory animals when administered systemically at relatively low dosage levels. The more potent corticosteroids have been shown to be teratogenic after dermal application in laboratory animals.

Animal reproduction studies have not been conducted with CIPRODEX® Otic. No adequate and well controlled studies have been performed in pregnant women. Caution should be exercised when CIPRODEX® Otic is used by a pregnant woman.

Nursing Mothers:

Ciprofloxacin and corticosteroids, as a class, appear in milk following oral administration. Dexamethasone in breast milk could suppress growth, interfere with endogenous corticosteroid production, or cause other untoward effects. It is not known whether topical otic administration of ciprofloxacin or dexamethasone could result in sufficient systemic absorption to produce detectable quantities in human milk. Because of the potential for unwanted effects in nursing infants, a decision should be made whether to discontinue nursing or to discontinue the drug, taking into account the importance of the drug to the mother.

Pediatric Use:

The safety and efficacy of CIPRODEX® Otic have been established in pediatric patients 6 months and older (937 patients) in adequate and well-controlled clinical trials. Although no data are available on patients less than age 6 months, there are no known safety concerns or differences in the disease process in this population that would preclude use of this product. (See DOSAGE AND ADMINISTRATION.)

No clinically relevant changes in hearing function were observed in 69 pediatric patients (age 4 to 12 years) treated with CIPRODEX® Otic and tested for audiometric parameters.

ADVERSE REACTIONS

In Phases II and III clinical trials, a total of 937 patients were treated with CIPRODEX® Otic. This included 400 patients with acute otitis media with tympanostomy tubes and 537 patients with acute otitis externa. The reported treatment-related adverse events are listed below:

Acute Otitis Media in pediatric patients with tympanostomy tubes

The following treatment-related adverse events occurred in 0.5% or more of the patients with non-intact tympanic membranes.

Adverse Event | Incidence (N=400)
Ear discomfort | 3.0%
Ear pain | 2.3%
Ear precipitate (residue) | 0.5%
Irritability | 0.5%
Taste perversion | 0.5%

The following treatment-related adverse events were each reported in a single patient: tympanostomy tube blockage; ear pruritus; tinnitus; oral moniliasis; crying; dizziness; and erythema.

Acute Otitis Externa

The following treatment-related adverse events occurred in 0.4% or more of the patients with intact tympanic membranes.

Adverse Event | Incidence (N=537)
Ear pruritus | 1.5%
Ear debris | 0.6%
Superimposed ear infection | 0.6%
Ear congestion | 0.4%
Ear pain | 0.4%
Erythema | 0.4%

The following treatment-related adverse events were each reported in a single patient: ear discomfort; decreased hearing; and ear disorder (tingling).

DOSAGE AND ADMINISTRATION

CIPRODEX® OTIC SHOULD BE SHAKEN WELL IMMEDIATELY BEFORE USE

CIPRODEX® Otic contains 3 mg (3000 ug/mL) ciprofloxacin and 1 mg/mL dexamethasone.

Acute Otitis Media in pediatric patients with tympanostomy tubes: The recommended dosage regimen for the treatment of acute otitis media in pediatric patients (age 6 months and older) through tympanostomy tubes is:

Four drops (0.14 mL, 0.42 mg ciprofloxacin, 0.14 mg dexamethasone) instilled into the affected ear twice daily for seven days. The suspension should be warmed by holding the bottle in the hand for one or two minutes to avoid dizziness, which may result from the instillation of a cold suspension. The patient should lie with the affected ear upward, and then the drops should be instilled. The tragus should then be pumped 5 times by pushing inward to facilitate penetration of the drops into the middle ear. This position should be maintained for 60 seconds. Repeat, if necessary, for the opposite ear. Discard unused portion after therapy is completed.

Acute Otitis Externa: The recommended dosage regimen for the treatment of acute otitis externa is: For patients (age 6 months and older): Four drops (0.14 mL, 0.42 mg ciprofloxacin, 0.14 mg dexamethasone) instilled into the affected ear twice daily for seven days. The suspension should be warmed by holding the bottle in the hand for one or two minutes to avoid dizziness, which may result from the instillation of a cold suspension. The patient should lie with the affected ear upward, and then the drops should be instilled. This position should be maintained for 60 seconds to facilitate penetration of the drops into the ear canal. Repeat, if necessary, for the opposite ear. Discard unused portion after therapy is completed.

HOW SUPPLIED

CIPRODEX® (ciprofloxacin 0.3% and dexamethasone 0.1%) Sterile Otic Suspension is supplied as follows: 7.5 mL fill in a DROP-TAINER® system. The DROP-TAINER® system consists

of a natural polyethylene bottle and natural plug, with a white polypropylene closure. Tamper evidence is provided with a shrink band around the closure and neck area of the package.

NDC 21695-969-75, 7.5 mL fill

Storage:

Store at controlled room temperature, 15°C to 30°C (59°F to 86°F). Avoid freezing. Protect from light.

Clinical Studies:

In a randomized, multicenter, controlled clinical trial, CIPRODEX® Otic dosed 2 times per day for 7 days demonstrated clinical cures in the per protocol analysis in 86% of AOMT patients compared to 79% for ofloxacin solution, 0.3%, dosed 2 times per day for 10 days. Among culture positive patients, clinical cures were 90% for CIPRODEX® Otic compared to 79% for ofloxacin solution, 0.3%. Microbiological eradication rates for these patients in the same clinical trial were 91% for CIPRODEX® Otic compared to 82% for ofloxacin solution, 0.3%. In 2 randomized multicenter, controlled clinical trials, CIPRODEX® Otic dosed 2 times per day for 7 days demonstrated clinical cures in 87% and 94% of per protocol evaluable AOE patients, respectively, compared to 84% and 89%, respectively, for otic suspension containing neomycin 0.35%, polymyxin B 10,000 IU/mL, and hydrocortisone 1.0% (neo/poly/HC). Among culture positive patients clinical cures were 86% and 92% for CIPRODEX® Otic compared to 84% and 89%, respectively, for neo/poly/HC. Microbiological eradication rates for these patients in the same clinical trials were 86% and 92% for CIPRODEX® Otic compared to 85% and 85%, respectively, for neo/poly/HC.

References:

1. Campoli-Richards DM, Monk JP, Price A, Benfield P, Todd PA, Ward A. Ciprofloxacin: A review of its antibacterial activity, pharmacokinetic properties and therapeutic use. Drugs 1988;35:373-447.

2. Loew D, Schuster O, and Graul E. Dose-dependent pharmacokinetics of dexamethasone. Eur J Clin Pharmacol 1986;30:225-230.

U.S. Patent Nos. 6,284,804; 6,359,016

Licensed to Alcon, Inc. by Bayer Schering Pharma AG.

CIPRODEX is a registered trademark of Bayer AG, licensed to Alcon, Inc by Bayer AG.

Rx Only

©2003, 2004, 2008, 2009 Alcon, Inc.

Revision date: 17 July 2003

Relabeled by: Rebel Distributors Corp

Thousand Oaks, CA 91320

PATIENT INFORMATION

CIPRODEX® (CI-PRO-DEX)

(ciprofloxacin 0.3% and dexamethasone 0.1%)

Sterile Otic Suspension

IMPORTANT PATIENT INFORMATION AND INSTRUCTIONS. READ BEFORE USE.

What is CIPRODEX® Otic?

CIPRODEX® Otic is an antibiotic/steroid combination product in a sterile suspension used to treat:

• Middle Ear Infection with Drainage Through a Tube in Children 6 months and older: A middle ear infection is a bacterial infection behind the eardrum. People with a tube in the eardrum may notice drainage from the ear canal.\

• Outer Ear Canal Infection in Patients 6 months and older: An outer ear canal infection, also known as "Swimmer's Ear", is a bacterial infection of the outer ear canal. The ear canal and the outer part of the ear may swell, turn red, and be painful. Also, a fluid discharge may appear in the ear canal.

Who should NOT use CIPRODEX® Otic?

• Do not use this product if allergic to ciprofloxacin or to other quinolone antibiotics.

• Do not use this product if allergic to dexamethasone or to other steroids.

• Do not give this product to pediatric patients who are less than 6 months old.

How often should CIPRODEX® Otic be given?

CIPRODEX® Otic ear drops should be given 2 times each day (about 12 hours apart, for example, 8 AM and 8 PM) in each infected ear unless the doctor has instructed otherwise. The best times to use the ear drops are in the morning and at night. It is very important to use the ear drops for as long as the doctor has instructed, even if the symptoms improve. If CIPRODEX® Otic ear drops are not used for as long as the doctor has instructed, the infection may return.

What if a dose is missed?

If a dose of CIPRODEX® Otic is missed, it should be given as soon as possible. If it is almost time for the next dose, skip the missed dose and go back to the regular dosing schedule. Do not use a double dose unless the doctor has instructed you to do so. If the infection is not improved after one week, you should consult your doctor. If you have two or more episodes of drainage within six months, it is recommended you see your doctor for further evaluation.

What activities should be avoided while using CIPRODEX® Otic?

It is important that the infected ear(s) remain clean and dry. When bathing, avoid getting the infected ear(s) wet. Avoid swimming unless the doctor has instructed otherwise.

What are the possible side effects of CIPRODEX® Otic?

During the testing of CIPRODEX® Otic for middle ear infections, the most common side effect related to CIPRODEX® Otic was ear discomfort that occurred in up to 3 out of 100 patients. Other common side effects were: ear pain; ear precipitate (residue); irritability; and abnormal taste. During the testing of CIPRODEX® Otic for ear canal infections, the most common side effect related to CIPRODEX® Otic was itching of the ear that occurred in 1 to 2 out of 100 patients. Other common side effects were: ear debris; ear infection in the treated ear; ear congestion; ear pain; and rash.

If any of these side effects persist, call the doctor.

If an allergic reaction to CIPRODEX® Otic occurs, stop using the product and contact your doctor.

DO NOT TAKE BY MOUTH

If CIPRODEX® Otic is accidentally swallowed or overdose occurs, call the doctor immediately. This medicine is available only with a doctor's prescription. Use only as directed. Do not use this medicine if outdated. If you wish to learn more about CIPRODEX® Otic, call your doctor or pharmacist.

HOW SUPPLIED

CIPRODEX® Otic is supplied as follows: 7.5 mL fill in a DROP-TAINER® system. The DROP-TAINER® system consists of a natural polyethylene bottle and natural plug, with a white polypropylene closure. Tamper evidence is provided with a shrink band around the closure and neck area of the package.

NDC 21695-969-75, 7.5 mL fill

Storage:

Store at controlled room temperature, 15°C to 30°C (59°F to 86°F). Avoid freezing. Protect from light.

U.S. Patent Nos. 6,284,804; 6,359,016

Licensed to Alcon, Inc. by Bayer Schering Pharma AG.

CIPRODEX is a registered trademark of Bayer AG, licensed to Alcon, Inc by Bayer AG.

Rx Only

©2003, 2004, 2008, 2009 Alcon, Inc.

Relabeled by: Rebel Distributors Corp

Thousand Oaks, CA 91320

How should CIPRODEX® Otic be given?

1. Wash hands

The person giving CIPRODEX® Otic should wash his/her hands with soap and water.

2. Warm & shake bottle

Hold the bottle of CIPRODEX® Otic in the hand for one or two minutes to warm the suspension, then shake well.

3. Add drops

The person receiving CIPRODEX® Otic should lie on his/her side with the infected ear up.

Patients should have 4 drops of CIPRODEX® Otic put into the infected ear. The tip of the bottle should not touch the fingers, or the ear, or any other surfaces.

BE SURE TO FOLLOW INSTRUCTIONS BELOW FOR THE PATIENT'S SPECIFIC EAR INFECTION.

4. For Patients with Middle Ear Infection with Tubes:

While the person receiving CIPRODEX® Otic lies on his/her side, the person giving the drops should gently press the tragus (see diagram) 5 times in a pumping motion. This will allow the drops to pass through the tube in the eardrum and into the middle ear.

5. For Patients with Outer Ear Infection ("Swimmer's Ear"):

While the person receiving the drops lies on his/her side, the person giving the drops should gently pull the outer ear lobe upward and backward. This will allow the ear drops to flow down into the ear canal.

6. Stay on side

The person who received the ear drops should remain on his/her side for at least 60 seconds.

Repeat Steps 2-5 for the other ear if both ears are infected.

345579-0709